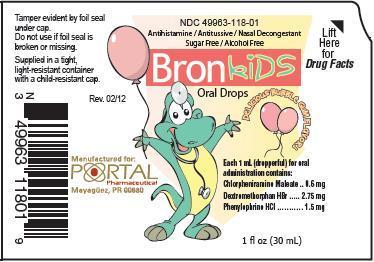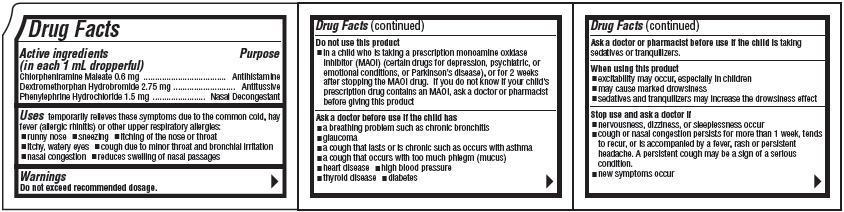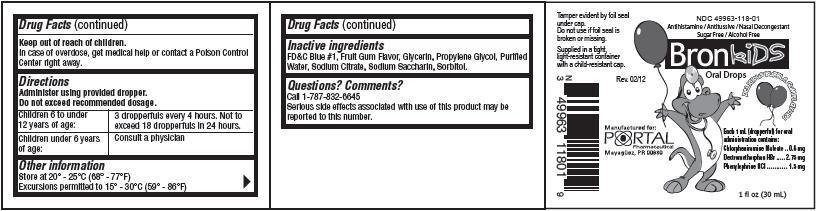 DRUG LABEL: Bronkids
                
NDC: 49963-118 | Form: LIQUID
Manufacturer: Portal Pharmaceutical
Category: otc | Type: HUMAN OTC DRUG LABEL
Date: 20121008

ACTIVE INGREDIENTS: Chlorpheniramine Maleate 0.6 mg/1 mL; Phenylephrine Hydrochloride 1.5 mg/1 mL; Dextromethorphan Hydrobromide 2.75 mg/1 mL
INACTIVE INGREDIENTS: Glycerin; Propylene Glycol; Water; Sodium Citrate; Saccharin Sodium; Sorbitol

Bronkids Oral Drops

Drug Facts

Active ingredients
(in each 1 mL dropperful)
Chlorpheniramine Maleate 0.6 mg
Dextromethorphan Hydrobromide 2.75 mg
Phenylephrine Hydrochloride 1.5 mg

PURPOSE

Antihistamine
Antitussive
Nasal Decongestant

Uses

temporarily relieves these symptoms due to the common cold, hay fever (allergic rhinitis) or other upper respiratory allergies:

- runny nose
- sneezing
- itching of the nose or throat
- itchy, watery eyes
- cough due to minor throat and bronchial irritation
- nasal congestion
- reduces swelling of nasal passages

Warnings

Do not exceed recommended dosage.

Do not use this product

- in a child who is taking a prescription monoamine oxidase inhibitor (MAOI) (certain drugs for depression, psychiatric, or emotional conditions, or Parkinson's disease), or for 2 weeks after stopping the MAOI drug. If you do not know if your child's prescription drug contains an MAOI, ask a doctor or pharmacist before giving this product.

Ask a doctor before use if the child has

- a breathing problem such as chronic bronchitis
- glaucoma
- a cough that lasts or is chronic such as occurs with asthma
- a cough that occurs with too much phlegm (mucus)
- heart disease
- high blood pressure
- thyroid disease
- diabetes

Ask a doctor or pharmacist before use if the child is taking sedatives or tranquilizers.

When using this product

- excitability may occur, especially in children
- may cause marked drowsiness
- sedatives and tranquilizers may increase the drowsiness effect

Stop use and ask a doctor if

- nervousness, dizziness, or sleeplessness occur
- cough or nasal congestion persists for more than 1 week, tends to recur, or is accompanied by a fever, rash or persistent headache. A persistent cough may be a sign of a serious condition
- new symptoms occur

Keep out of reach of children.

In case of overdose, get medical help or contact a Poison Control Center right away.

Directions

Administer using provided dropper.
Do not exceed recommended dosage.

Children 6 to under 12 years of age: | 3 dropperfuls every 4 hours. Not to exceed 18 dropperfuls in 24 hours.
Children under 6 years of age: | Consult a physician

Other information

Store at 20°-25°C (68°-77°F)
Excursions permitted to 15°-30°C (59°-86°F)

Inactive ingredients

FD&C Blue #1, Fruit Gum Flavor, Glycerin, Propylene Glycol, Purified Water, Sodium Citrate, Sodium Saccharin, Sorbitol.

Questions? Comments?

Call 1-787-832-6645
Serious side effects associated with use of this product may be reported to this number.

Product Packaging

Packaging below represents the labeling currently used.
Principal display panel and side panel for 30 mL label:
NDC 49963-118-01
Antihistamine / Antitussive / Nasal Decongestant
Sugar Free / Alcohol Free
Bronkids Oral Drops
DELICIOUS BUBBLE GUM FLAVOR!
Each 1 mL (dropperful) for oral administration contains:
Chlorpheniramine Maleate.......................0.6 mg
Dextromethorphan HBr..........................2.75 mg
Phenylephrine HCl..................................1.5 mg
1 fl oz (30 mL)
Tamper evident by foil seal under cap.
Do not use if foil seal is broken or missing.
Supplied in a tight, light-resistant container
with a child-resistant cap.
Rev. 02/12
Manufactured for:
PORTAL Pharmaceutical
Mayaguez, PR 00680